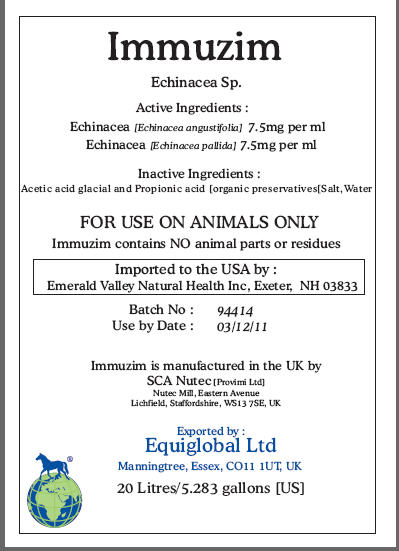 DRUG LABEL: Immuzim
NDC: 52338-398 | Form: EXTRACT
Manufacturer: SCA NuTec
Category: animal | Type: PRESCRIPTION ANIMAL DRUG LABEL
Date: 20100419

ACTIVE INGREDIENTS: ECHINACEA ANGUSTIFOLIA ROOT 7.5 1/1 mL; ECHINACEA PALLIDA ROOT 7.5 1/1 mL

Immuzim

Echinacea Sp.

Active Ingredients:

Echinacea [Echinacea angustifolia] 7.5mg per ml
Echinacea [Echinacea pallida] 7.5mg per ml

Inactive Ingredients:

Acetic acid glacial and Propionic acid [organic preservatives[Salt,Water

WARNINGS

FOR USE ON ANIMALS ONLY

Immuzim contains NO animal parts or residues

Imported to the USA by :
Emerald Valley Natural Health Inc, Exeter, NH 03833
Batch No: 94414
Use by Date: 03/12/11
Immuzim is manufactured in the UK by
SCA Nutec [Provimi Ltd]
Nutec Mill, Eastern Avenue
Lichfield, Staffordshire, WS13 7SE, UK
Exported by :
Equiglobal Ltd
Manningtree, Essex, CO11 1UT, UK
20 Litres/5.283 gallons [US]